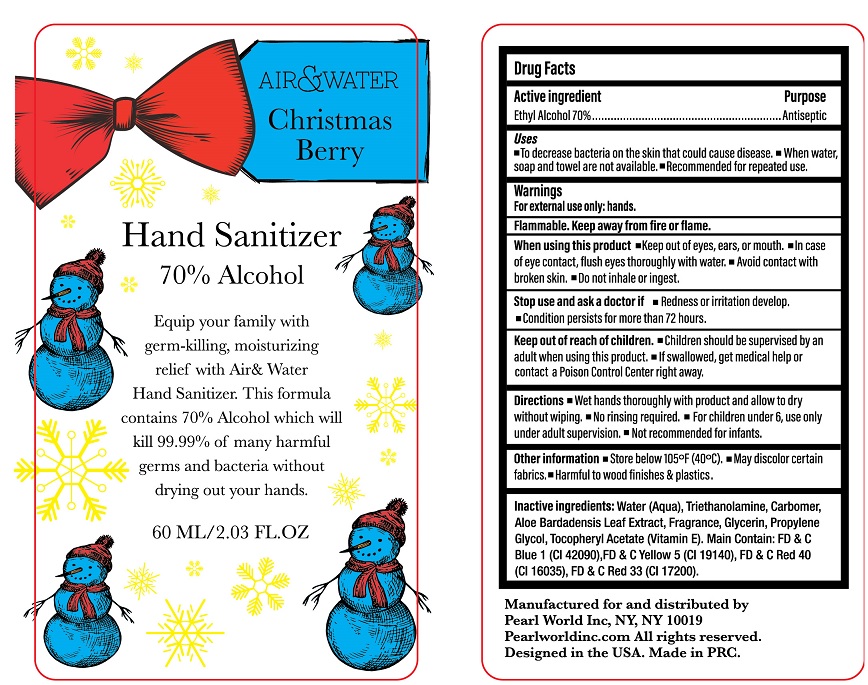 DRUG LABEL: Air and Water Christmas Berry Hand Sanitizer
NDC: 74149-042 | Form: LIQUID
Manufacturer: Yiwu Yangjie Daily Chemicals Co.,Ltd.
Category: otc | Type: HUMAN OTC DRUG LABEL
Date: 20201218

ACTIVE INGREDIENTS: ALCOHOL 70 mL/100 mL
INACTIVE INGREDIENTS: WATER; GLYCERIN; TROLAMINE; PROPYLENE GLYCOL; ALPHA-TOCOPHEROL

Drug facts

Active ingredient Ethyl Alcohol ........... 70% v/v

PURPOSE

Antiseptic

KEEP OUT OF REACH OF CHILDREN

If swallowed, get medical help or contact a poison control center right away.

INDICATIONS AND USAGE

- To decrease bacteria on the skin that could cause disease
- When water, soap and towel are not available.
- recommended for repeated use

WARNINGS

For external use only
Flammable. Keep away from fire or flame.

When using this product

- Keep out of eyes, ears or mouth
- In case of eye contact, flush eyes with water.
- Avoid contact with broken skin.
- Do not inhale or ingest

Stop use and ask a doctor If

- Redness or irritation develops.
- Condition persists for more than 72 hours

Other information:

- Store under 105℉ (40℃).
- May discolor certain fabrics.
- Harmful to wood finishes and plastics.

Directions:

- Wet hands thoroughly with product and allow to dry without wiping.
- No rinsing required.
- For children under 6, use only under adult supervision.
- Not recommended for infants.

INACTIVE INGREDIENT

Water (Aqua), Triethanolamine, Carbomer, Aloe Bardadensis Leaf Extract, Fragrance, Glycerin, Propylene Glycol, Tocopheryl Acetate (Vitamin E). Main Contain: FD & C Red 40 (Cl 16035), FD & C Yellow 6 (Cl 15985), FD& C Violet 2 (Cl 60725), FD& C Blue 1 (Cl 42090), FD & C Yellow 5 (Cl 19140), FD& C Red 33 (Cl 17200).